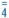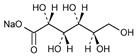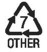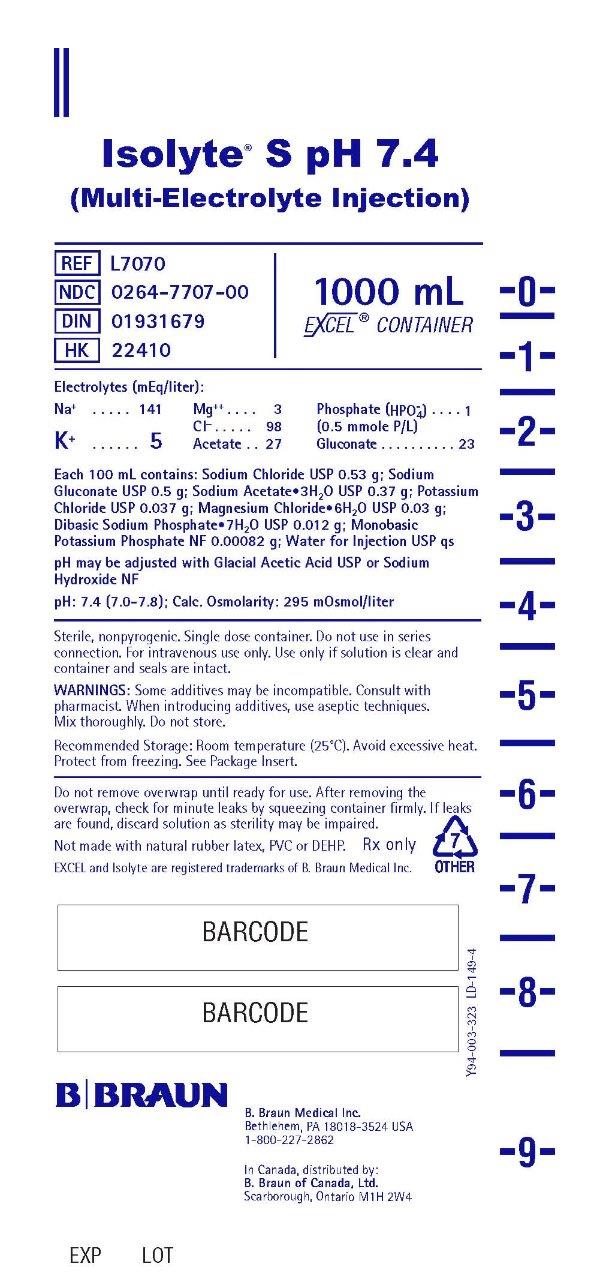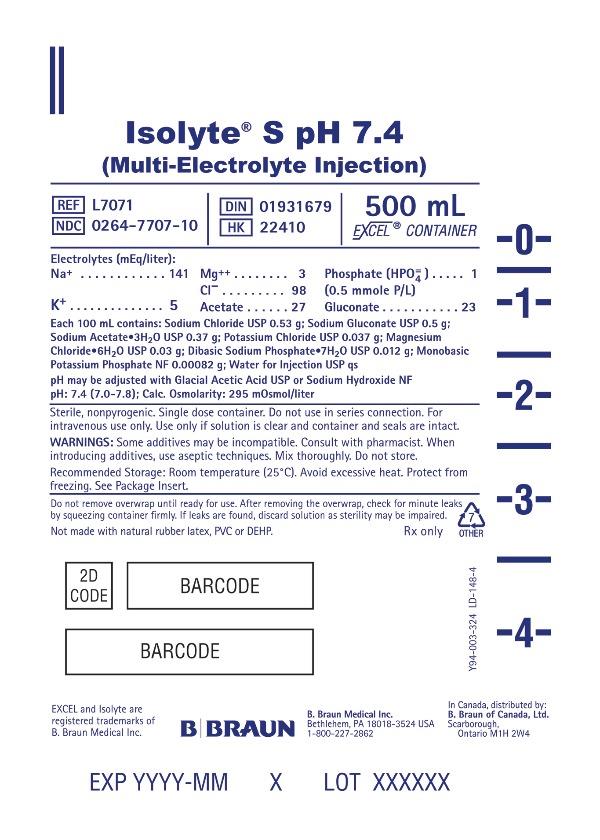 DRUG LABEL: Isolyte S pH 7.4
NDC: 0264-7707 | Form: INJECTION, SOLUTION
Manufacturer: B. Braun Medical Inc.
Category: prescription | Type: HUMAN PRESCRIPTION DRUG LABEL
Date: 20231006

ACTIVE INGREDIENTS: SODIUM CHLORIDE 0.53 g/100 mL; SODIUM GLUCONATE 0.5 g/100 mL; SODIUM ACETATE 0.37 g/100 mL; POTASSIUM CHLORIDE 0.037 g/100 mL; MAGNESIUM CHLORIDE 0.03 g/100 mL; SODIUM PHOSPHATE, DIBASIC 0.012 g/100 mL; POTASSIUM PHOSPHATE, MONOBASIC 0.00082 g/100 mL
INACTIVE INGREDIENTS: WATER

Isolyte® S pH 7.4
(Multi-Electrolyte Injection)

DESCRIPTION

Each 100 mL of Isolyte® S pH 7.4 (Multi-Electrolyte Injection) contains:
Sodium Chloride USP 0.53 g; Sodium Gluconate USP 0.5 g
Sodium Acetate Trihydrate USP 0.37 g; Potassium Chloride USP 0.037 g
Magnesium Chloride Hexahydrate USP 0.03 g
Dibasic Sodium Phosphate Heptahydrate USP 0.012 g
Monobasic Potassium Phosphate NF 0.00082 g; Water for Injection USP qs
pH may be adjusted with Glacial Acetic Acid USP or Sodium Hydroxide NF
pH: 7.4 (7.0–7.8) Calculated Osmolarity: 295 mOsmol/liter
Concentration of Electrolytes (mEq/liter): Sodium 141; Potassium 5
Magnesium 3; Chloride 98; [0.5 mmole P/liter] Phosphate (HPO) 1; Acetate (CH3COO^–) 27 Gluconate (HOCH2(CHOH)4COO^–) 23

Isolyte® S pH 7.4 is sterile, nonpyrogenic, and contains no bacteriostatic or antimicrobial agents. This product is intended for intravenous administration.

The formulas of the active ingredients are:

Ingredients | Molecular Formula | Molecular Weight
Sodium Chloride USP | NaCl | 58.44
Sodium Acetate Trihydrate USP | CH3COONa•3H2O | 136.08
Potassium Chloride USP | KCl | 74.55
Magnesium Chloride Hexahydrate USP | MgCl2•6H2O | 203.30
Dibasic Sodium Phosphate Heptahydrate USP | Na2HPO4•7H2O | 268.07
Monobasic Potassium Phosphate NF | KH2PO4 | 136.09
Sodium Gluconate USP |  | 218.14

Not made with natural rubber latex, PVC or DEHP.

The plastic container is made from a multilayered film specifically developed for parenteral drugs. It contains no plasticizers and exhibits virtually no leachables. The solution contact layer is a rubberized copolymer of ethylene and propylene. The container is nontoxic and biologically inert. The container-solution unit is a closed system and is not dependent upon entry of external air during administration. The container is overwrapped to provide protection from the physical environment and to provide an additional moisture barrier when necessary.

Addition of medication should be accomplished using complete aseptic technique.

The closure system has two ports; the one for the administration set has a tamper evident plastic protector and the other is a medication addition site. Refer to the Directions for Use of the container.

CLINICAL PHARMACOLOGY

Isolyte® S pH 7.4 provides electrolytes and is a source of water for hydration. It is capable of inducing diuresis depending on the clinical condition of the patient.

Sodium, the major cation of the extracellular fluid, functions primarily in the control of water distribution, fluid balance, and osmotic pressure of body fluids. Sodium is also associated with chloride and bicarbonate in the regulation of the acid-base equilibrium of body fluid.

Potassium, the principal cation of intracellular fluid, participates in carbohydrate utilization and protein synthesis, and is critical in the regulation of nerve conduction and muscle contraction, particularly in the heart.

Chloride, the major extracellular anion, closely follows the metabolism of sodium, and changes in the acid-base balance of the body are reflected by changes in the chloride concentration.

Phosphate is a major intracellular anion which participates in providing energy for metabolism of substrates and contributes to significant metabolic and enzymatic reactions in almost all organs and tissues. It exerts a modifying influence on calcium levels, a buffering effect on acid-base equilibrium and has a primary role in the renal excretion of hydrogen ions.

Magnesium, a principal cation of soft tissue, is primarily involved in enzyme activity associated with the metabolism of carbohydrates and protein. Magnesium is also involved in neuromuscular irritability.

Gluconate and acetate are organic ions which are hydrogen ion acceptors and contribute bicarbonate during their metabolism to carbon dioxide and water, and serve as alkalinizing agents.

INDICATIONS AND USAGE

This solution is indicated for use in adults as a source of electrolytes and water for hydration, and as an alkalinizing agent.

CONTRAINDICATIONS

Contraindications: None known. Accurate clinical and laboratory estimation of fluid and electrolyte balance in order to access benefit/risk ratio are essential prior to administration of this solution (see WARNINGS and PRECAUTIONS).

WARNINGS

The administration of intravenous solutions can cause fluid and/or solute overload resulting in dilution of serum electrolyte concentrations, overhydration, congested states or pulmonary edema. The risk of dilutional states is inversely proportional to the electrolyte concentration. The risk of solute overload causing congested states with peripheral and pulmonary edema is directly proportional to the electrolyte concentration.

Solutions containing sodium ions should be used with great care, if at all, in patients with congestive heart failure, severe renal insufficiency, and in clinical states in which there is sodium retention with edema.

In patients with diminished renal function, administration of solutions containing sodium or potassium ions may result in sodium or potassium retention.

Solutions containing potassium ions should be used with great care, if at all, in patients with hyperkalemia, severe renal failure, and in conditions in which potassium retention is present.

Solutions containing gluconate or acetate should be used with great care in patients with metabolic or respiratory alkalosis and in those conditions in which there is an increased level or an impaired utilization of these ions, such as severe hepatic insufficiency.

PRECAUTIONS

General

This solution should be used with care in patients with hypervolemia, renal insufficiency, urinary tract obstruction, or impending or frank cardiac decompensation.

Extraordinary electrolyte losses such as may occur during protracted nasogastric suction, vomiting, diarrhea or gastrointestinal fistula drainage may necessitate additional electrolyte supplementation.

Additional essential electrolytes, minerals, and vitamins should be supplied as needed.

Care should be exercised in administering solutions containing sodium or potassium to patients with renal or cardiovascular insufficiency, with or without congestive heart failure, particularly if they are postoperative or elderly.

Potassium therapy should be guided primarily by serial electrocardiograms, especially in patients receiving digitalis. Serum potassium levels are not necessarily indicative of tissue potassium levels.

Solutions containing potassium or magnesium should be used with caution in the presence of cardiac disease, particularly when accompanied by renal disease.

Solutions containing gluconate or acetate should be used with caution. Excess administration may result in metabolic alkalosis.

To minimize the risk of possible incompatibilities arising from mixing this solution with other additives that may be prescribed, the final infusate should be inspected for cloudiness or precipitation immediately after mixing, prior to administration, and periodically during administration.

Do not use plastic containers in series connection.

If administration is controlled by a pumping device, care must be taken to discontinue pumping action before the container runs dry or air embolism may result. If administration is not controlled by a pumping device, refrain from applying excessive pressure (>300mmHg) causing distortion to the container such as wringing or twisting. Such handling could result in breakage of the container.

This solution is intended for intravenous administration using sterile equipment. It is recommended that intravenous administration apparatus be replaced at least once every 24 hours.

Use only if solution is clear and container and seals are intact.

Laboratory Tests

Clinical evaluation and periodic laboratory determinations are necessary to monitor changes in fluid balance, electrolyte concentrations, and acid-base balance during prolonged parenteral therapy or whenever the condition of the patient warrants such evaluation. Significant deviations from normal concentrations may require tailoring of the electrolyte pattern, in this or an alternative solution.

Drug Interactions

Sodium-containing solutions should be administered with caution to patients receiving corticosteroids or corticotropin, or to other salt-retaining patients.

Administration of barbiturates, narcotics, hypnotics or systemic anesthetics should be adjusted with caution in patients also receiving magnesium-containing solutions because of an additive central depressive effect.

Parenteral magnesium should be administered with extreme caution to patients receiving digitalis preparations.

Carcinogenesis, Mutagenesis, Impairment of Fertility

Long term animal studies with Isolyte® S pH 7.4 (Multi-Electrolyte Injection) have not been performed to evaluate the carcinogenic potential, mutagenic potential, or effects on fertility.

Pregnancy

Teratogenic Effects

Animal reproduction studies have not been conducted with Isolyte® S pH 7.4 (Multi-Electrolyte Injection). It is also not known whether Isolyte® S pH 7.4 can cause fetal harm when administered to a pregnant woman or can affect reproduction capacity. Isolyte® S pH 7.4 should be given to a pregnant woman only if clearly needed.

Labor and Delivery

As reported in the literature, electrolyte solutions have been administered during labor and delivery. Caution should be exercised, and the fluid balance, glucose and electrolyte concentrations, and acid-base balance, of both mother and fetus should be evaluated periodically or whenever warranted by the condition of the patient or fetus.

Nursing Mothers

Caution should be exercised when Isolyte® S pH 7.4 (Multi-Electrolyte Injection) is administered to a nursing woman.

Pediatric Use

Safety and effectiveness in pediatric patients have not been established.

Geriatric Use

In general, dose selection for an elderly patient should be cautious, usually starting at the low end of the dosing range, reflecting the greater frequency of decreased hepatic, renal, or cardiac function, and of concomitant disease or other drug therapy.

This drug is known to be substantially excreted by the kidney, and the risk of toxic reactions to this drug may be greater in patients with impaired renal function. Because elderly patients are more likely to have decreased renal function, care should be taken in dose selection, and it may be useful to monitor renal function.

See WARNINGS.

ADVERSE REACTIONS

Reactions which may occur because of the solution or the technique of administration include febrile response, infection at the site of injection, venous thrombosis or phlebitis extending from the site of injection, extravasation and hypervolemia.

Symptoms may result from an excess or deficit of one or more of the ions present in the solution; therefore, frequent monitoring of electrolyte levels is essential.

Hypernatremia may be associated with edema and exacerbation of congestive heart failure due to the retention of water, resulting in an expanded extracellular fluid volume.

Reactions reported with the use of potassium-containing solutions include nausea, vomiting, abdominal pain and diarrhea. The signs and symptoms of potassium intoxication include paresthesias of the extremities, areflexia, muscular or respiratory paralysis, mental confusion, weakness, hypotension, cardiac arrhythmias, heart block, electrocardiographic abnormalities and cardiac arrest. Potassium deficits result in disruption of neuromuscular function, and intestinal ileus and dilatation.

If infused in large amounts, chloride ions may cause a loss of bicarbonate ions, resulting in an acidifying effect.

Phosphorus deficiency may lead to impaired tissue oxygenation and acute hemolytic anemia. Relative to calcium, excessive phosphorus intake can precipitate hypocalcemia with cramps, tetany and muscular hyperexcitability.

Abnormally high plasma levels of magnesium can result in flushing, sweating, hypotension, circulatory collapse, and depression of cardiac and central nervous system function. Respiratory depression is the most immediate threat to life. Magnesium deficits can result in tachycardia, hypertension, hyperirritability and psychotic behavior.

The physician should also be alert to the possibility of adverse reactions to drug additives. Prescribing information for drug additives to be administered in this manner should be consulted.

If an adverse reaction does occur, discontinue the infusion, evaluate the patient, institute appropriate therapeutic countermeasures and save the remainder of the fluid for examination if deemed necessary.

OVERDOSAGE

In the event of a fluid or solute overload during parenteral therapy, reevaluate the patient's condition, and institute appropriate corrective treatment.

In the event of overdosage with potassium-containing solutions, discontinue the infusion immediately and institute corrective therapy to reduce serum potassium levels.

Treatment of hyperkalemia includes the following:

1. Dextrose Injection USP, 10% or 25%, containing 10 units of crystalline insulin per 20 grams of dextrose administered intravenously, 300 to 500 mL per hour.
2. Absorption and exchange of potassium using sodium or ammonium cycle cation exchange resin, orally and as retention enema.
3. Hemodialysis and peritoneal dialysis. The use of potassium-containing foods or medications must be eliminated. However, in cases of digitalization, too rapid a lowering of plasma potassium concentration can cause digitalis toxicity.

Over-aggressive phosphate replacement may precipitate hypocalcemic tetany. To prevent hypocalcemia, calcium supplementation should always accompany phosphate administration.

DOSAGE AND ADMINISTRATION

This solution is for intravenous use only.

Dosage is to be directed by a physician and is dependent upon age, weight, clinical condition of the patient and laboratory determinations. Frequent laboratory determinations and clinical evaluation are essential to monitor changes in blood glucose and electrolyte concentrations, and fluid and electrolyte balance during prolonged parenteral therapy.

Fluid administration should be based on calculated maintenance or replacement fluid requirements for each patient.

Isolyte® S pH 7.4 (Multi-Electrolyte Injection) may be admixed with solutions which contain phosphate or which have been supplemented with phosphate.

The presence of magnesium and phosphate ions in this solution should be considered when phosphate is present in the additive solution, in order to avoid precipitation.

Some additives may be incompatible. Consult with pharmacist. When introducing additives, use aseptic techniques. Mix thoroughly. Do not store.

Parenteral drug products should be inspected visually for particulate matter and discoloration prior to administration, whenever solution and container permit.

HOW SUPPLIED

Isolyte® S pH 7.4 (Multi-Electrolyte Injection) is supplied sterile and nonpyrogenic in EXCEL® Containers. The 1000 mL containers are packaged 12 per case and the 500 mL containers are packaged 24 per case.

NDC | REF | Size
Isolyte® S pH 7.4 (Multi-Electrolyte Injection)
(Canada DIN 01931679)
0264-7707-00 | L7070 | 1000 mL
0264-7707-10 | L7071 | 500 mL

STORAGE AND HANDLING

Exposure of pharmaceutical products to heat should be minimized. Avoid excessive heat. Protect from freezing. It is recommended that the product be stored at room temperature (25°C); however, brief exposure up to 40°C does not adversely affect the product.

Rx only

Revised: July 2018

EXCEL and Isolyte are registered trademarks of B. Braun Medical Inc.

Directions for Use of EXCEL® Container

Caution: Do not use plastic containers in series connection.

To Open

Tear overwrap down at notch and remove solution container. Check for minute leaks by squeezing solution container firmly. If leaks are found, discard solution as sterility may be impaired. If supplemental medication is desired, follow directions below before preparing for administration.

NOTE: Before use, perform the following checks:

- Inspect each container. Read the label. Ensure solution is the one ordered and is within the expiration date.
- Invert container and carefully inspect the solution in good light for cloudiness, haze, or particulate matter. Any container which is suspect should not be used.
- Use only if solution is clear and container and seals are intact.

Preparation for Administration

1. Remove plastic protector from sterile set port at bottom of container.
2. Attach administration set. Refer to complete directions accompanying set.

To Add Medication

Warning: Some additives may be incompatible.

To Add Medication Before Solution Administration

1. Prepare medication site.
2. Using syringe with 18–22 gauge needle, puncture medication port and inner diaphragm and inject.
3. Squeeze and tap ports while ports are upright and mix solution and medication thoroughly.

To Add Medication During Solution Administration

1. Close clamp on the set.
2. Prepare medication site.
3. Using syringe with 18–22 gauge needle of appropriate length (at least 5/8 inch), puncture resealable medication port and inner diaphragm and inject.
4. Remove container from IV pole and/or turn to an upright position.
5. Evacuate both ports by tapping and squeezing them while container is in the upright position.
6. Mix solution and medication thoroughly.
7. Return container to in use position and continue administration.

B. Braun Medical Inc.
Bethlehem, PA 18018-3524 USA
1-800-227-2862

In Canada, distributed by:
B. Braun of Canada, Ltd.
Scarborough, Ontario M1H 2W4

Y36-002-952 LD-490-3

PRINCIPAL DISPLAY PANEL - 1000 mL Container Label

Isolyte® S pH 7.4
(Multi-Electrolyte Injection)

REF L7070
NDC 0264-7707-00
DIN 01931679
HK 22410

1000 mL
EXCEL® CONTAINER

Electrolytes (mEq/liter):

Na^+ 141
K^+ 5
Mg^++ 3
Cl^– 98
Acetate 27
Phosphate
(HPO) 1
(0.5 mmole P/L)
Gluconate 23

Each 100 mL contains: Sodium Chloride USP 0.53 g; Sodium
Gluconate USP 0.5 g; Sodium Acetate•3H2O USP 0.37 g; Potassium
Chloride USP 0.037 g; Magnesium Chloride•6H2O USP 0.03 g;
Dibasic Sodium Phosphate•7H2O USP 0.012 g; Monobasic
Potassium Phosphate NF 0.00082 g; Water for Injection USP qs

pH may be adjusted with Glacial Acetic Acid USP or Sodium
Hydroxide NF

pH: 7.4 (7.0-7.8); Calc. Osmolarity: 295 mOsmol/liter

Sterile, nonpyrogenic. Single dose container. Do not use in series
connection. For intravenous use only. Use only if solution is clear and
container and seals are intact.

WARNINGS: Some additives may be incompatible. Consult with
pharmacist. When introducing additives, use aseptic techniques.
Mix thoroughly. Do not store.

Recommended Storage: Room temperature (25°C). Avoid excessive heat.
Protect from freezing. See Package Insert.

Do not remove overwrap until ready for use. After removing the
overwrap, check for minute leaks by squeezing container firmly. If leaks
are found, discard solution as sterility may be impaired.

Not made with natural rubber latex, PVC or DEHP.

Rx only

EXCEL and Isolyte are registered trademarks of B. Braun Medical Inc.

B. Braun Medical Inc.
Bethlehem, PA 18018-3524 USA
1-800-227-2862

In Canada, distributed by:
B. Braun of Canada, Ltd.
Scarborough, Ontario M1H 2W4

Y94-003-323
LD-149-4

EXP
LOT

PRINCIPAL DISPLAY PANEL - 500 mL Container Label

Isolyte® S pH 7.4
(Multi-Electrolyte Injection)

REF L7071
NDC 0264-7707-10

DIN 01931679
HK 22410

500 mL
EXCEL® CONTAINER

Electrolytes (mEq/liter):

Na^+ 141
K^+ 5
Mg^++ 3
Cl^– 98
Acetate 27
Phosphate
(HPO) 1
(0.5 mmole P/L)
Gluconate 23

Each 100 mL contains: Sodium Chloride USP 0.53 g; Sodium Gluconate USP 0.5 g;
Sodium Acetate•3H2O USP 0.37 g; Potassium Chloride USP 0.037 g; Magnesium
Chloride•6H2O USP 0.03 g; Dibasic Sodium Phosphate•7H2O USP 0.012 g; Monobasic
Potassium Phosphate NF 0.00082 g; Water for Injection USP qs

pH may be adjusted with Glacial Acetic Acid USP or Sodium Hydroxide NF
p H: 7.4 (7.0–7.8); Calc. Osmolarity: 295 mOsmol/liter

Sterile, nonpyrogenic. Single dose container. Do not use in series connection. For
intravenous use only. Use only if solution is clear and container and seals are intact.

WARNINGS: Some additives may be incompatible. Consult with pharmacist. When
introducing additives, use aseptic techniques. Mix thoroughly. Do not store.

Recommended Storage: Room temperature (25°C). Avoid excessive heat. Protect from
freezing. See Package Insert.

Do not remove overwrap until ready for use. After removing the overwrap, check for minute leaks
by squeezing container firmly. If leaks are found, discard solution as sterility may be impaired.

Not made with natural rubber latex, PVC or DEHP.

Rx only

EXCEL and Isolyte are registered trademarks of B. Braun Medical Inc.

B. Braun Medical Inc.
Bethlehem, PA 18018-3524 USA
1-800-227-2862

In Canada, distributed by:
B. Braun of Canada, Ltd.
Scarborough, Ontario M1H 2W4

Y94-003-324
LD-148-4

EXP
LOT